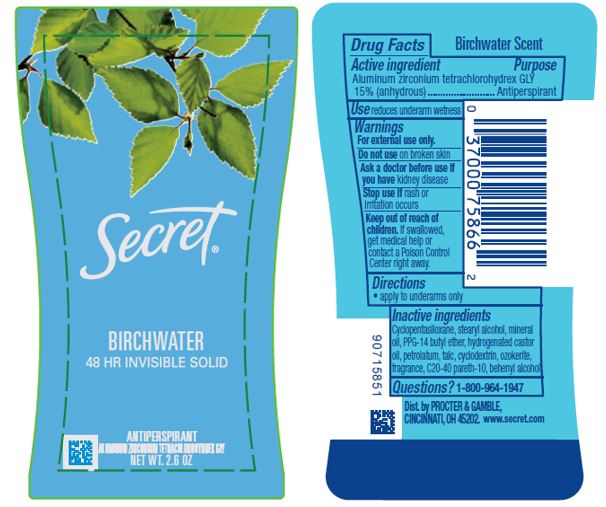 DRUG LABEL: Secret Birchwater Invisible
NDC: 69423-373 | Form: STICK
Manufacturer: The Procter & Gamble Manufacturing Company
Category: otc | Type: HUMAN OTC DRUG LABEL
Date: 20200206

ACTIVE INGREDIENTS: ALUMINUM ZIRCONIUM TETRACHLOROHYDREX GLY 15 g/100 g
INACTIVE INGREDIENTS: DOCOSANOL; CYCLOMETHICONE 5; PETROLATUM; STEARYL ALCOHOL; MINERAL OIL; CERESIN; TALC; HYDROGENATED CASTOR OIL; PPG-14 BUTYL ETHER; C20-40 PARETH-10; BETADEX

Secret Birchwater Invisible

Drug Facts

Active ingredient

Aluminum zirconium tetrachlorohydrex Gly 15% (anhydrous)

Purpose

Antiperspirant

Use

reduces underarm wetness

Warnings

For external use only.

Do not use on broken skin

Ask a doctor before use if you have kidney disease

Stop use if rash or irritation occurs

Keep out of reach of children. If swallowed, get medical help or contact a Poison Control Center right away.

Directions

apply to underarms only

Inactive ingredients

Cyclopentasiloxane, stearyl alcohol, mineral oil, PPG-14 butyl ether, hydrogenated castor oil, petrolatum, talc, cyclodextrin, ozokerite, fragrance, C20-40 pareth-10, behenyl alcohol

Questions?

1-800-964-1947

Dist. by PROCTER & GAMBLE,
CINCINNATI, OH 45202.

PRINCIPAL DISPLAY PANEL - 73 g Cylinder Label

Secret®

Birchwater

48 HR INVISIBLE SOLID

ANTIPERSPIRANT

ALUMINUM ZIRCONIUM TETRACHLOROHYDREX GLY
NET WT. 2.6 OZ (73 g)